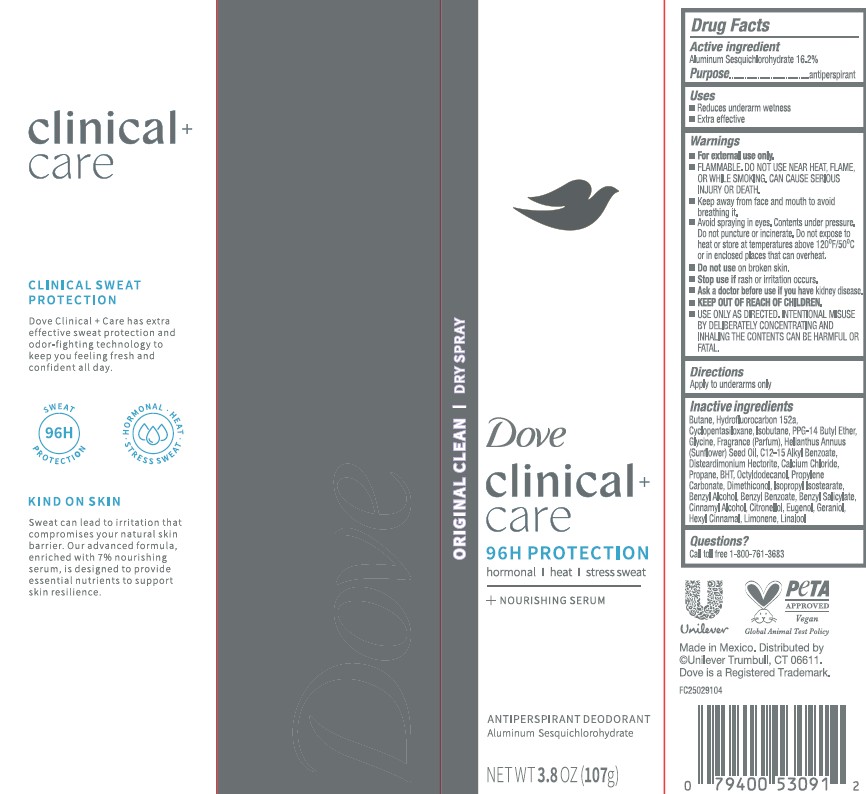 DRUG LABEL: Dove Clinical Care
NDC: 64942-2386 | Form: AEROSOL, SPRAY
Manufacturer: Conopco d/b/a Unilever
Category: otc | Type: HUMAN OTC DRUG LABEL
Date: 20251113

ACTIVE INGREDIENTS: ALUMINUM SESQUICHLOROHYDRATE 16.2 g/100 g
INACTIVE INGREDIENTS: DIMETHICONOL (40 CST); CYCLOPENTASILOXANE; BUTANE; BENZYL BENZOATE; LIMONENE, (+)-; EUGENOL; BENZYL SALICYLATE; BHT; DISTEARDIMONIUM HECTORITE; OCTYLDODECANOL; LINALOOL; HEXYL CINNAMAL; PROPANE; CINNAMYL ALCOHOL; GLYCINE; C12-15 ALKYL BENZOATE; CALCIUM CHLORIDE; HYDROFLUOROCARBON 152A; PROPYLENE CARBONATE; PPG-14 BUTYL ETHER; ISOPROPYL ISOSTEARATE; BENZYL ALCOHOL; CITRONELLOL; GERANIOL; ISOBUTANE; HELIANTHUS ANNUUS (SUNFLOWER) SEED OIL

Dove Clinical + Care 96H Protection Original Clean Dry Spray Antiperspirant Deodorant

DESCRIPTION

Dove Clinical + Care 96H Protection Original Clean Dry Spray Antiperspirant Deodorant

ACTIVE INGREDIENT

Aluminum Sesquichlorohydrate 16.2%

PURPOSE

antiperspirant

INDICATIONS AND USAGE

reduces underarm wetness

extra effective

WARNINGS

• For external use only. • FLAMMABLE. DO NOT USE NEAR HEAT, FLAME, OR WHILE
SMOKING. CAN CAUSE SERIOUS INJURY OR DEATH. • Keep away from face and mouth to avoid breathing it.
• Avoid spraying in eyes. Contents under pressure. Do not puncture or incinerate. Do not expose to heat or
store at temperatures above 120ºF/50ºC or in enclosed places that can overheat. • Do not use on broken skin. • Stop use if rash or irritation occurs. • Ask a doctor before use if you have kidney disease. • USE ONLY AS DIRECTED. INTENTIONAL MISUSE BY DELIBERATELY CONCENTRATING AND INHALING THE CONTENTS CAN BE HARMFUL OR FATAL

KEEP OUT OF REACH OF CHILDREN

DOSAGE AND ADMINISTRATION

apply to underarms only

INACTIVE INGREDIENT

Butane, Hydrofluorocarbon 152A, Cyclopentasiloxane, Isobutane, PPG-14 Butyl Ether, Glycine, Helianthus Annuus (Sunflower) Seed Oil, C12-15 Alkyl Benzoate, Disteardimonium Hectorite, Calcium Chloride, Propane, BHT, Octyldodecanol, Propylene Carbonate, Dimethiconol, Isopropyl Isostearate, Benzyl Alcohol, Benzyl Benzoate, Benzyl Salicylate, Cinnamyl Alcohol, Citronellol, Eugenol, Geraniol, Hexyl Cinnamal, Limonene, Linalool

QUESTIONS

Call toll-free 1-800-761-3683